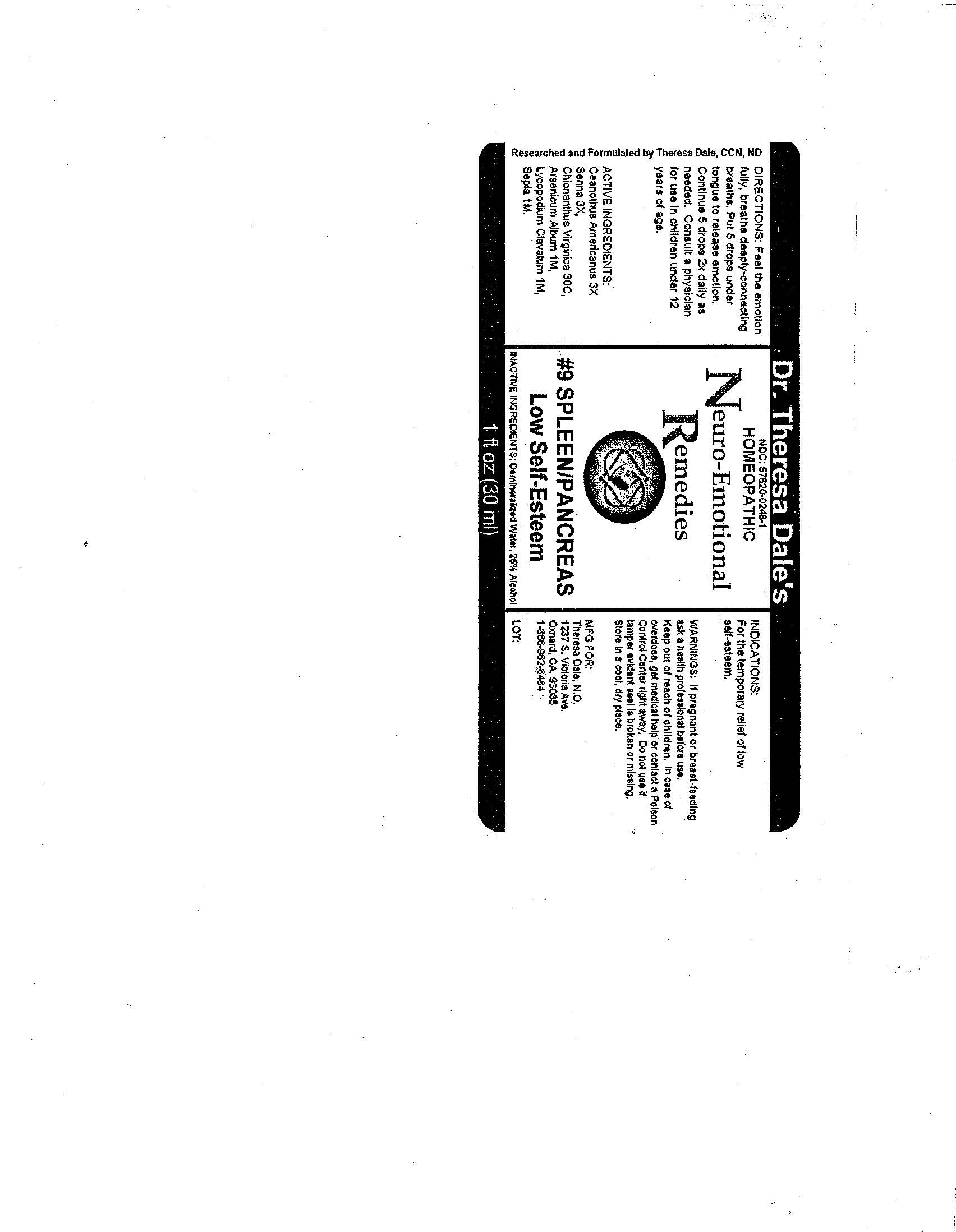 DRUG LABEL: 9 Spleen Pancreas
NDC: 57520-0248 | Form: LIQUID
Manufacturer: Apotheca Company
Category: homeopathic | Type: HUMAN OTC DRUG LABEL
Date: 20100802

ACTIVE INGREDIENTS: CEANOTHUS AMERICANUS LEAF 3 [hp_X]/1 mL; SENNA LEAF 3 [hp_X]/1 mL; CHIONANTHUS VIRGINICUS BARK 30 [hp_C]/1 mL; ARSENIC TRIOXIDE 1 [hp_M]/1 mL; LYCOPODIUM CLAVATUM SPORE 1 [hp_M]/1 mL; SEPIA OFFICINALIS JUICE 1 [hp_M]/1 mL
INACTIVE INGREDIENTS: WATER; ALCOHOL

#9 Spleen/Pancreas

ACTIVE INGREDIENT

ACTIVE INGREDIENTS: Ceanothus americanus 3X, Senna 3X, Chionanthus virginica 30C, Arsenicum album 1M, Lycopodium clavatum 1M, Sepia 1M.

PURPOSE

INDICATIONS: For the temporary relief of low self-esteem.

WARNINGS

WARNINGS: If pregnant or breast-feeding, ask a health professional before use.

Keep out of reach of children. In case of overdose, get medical help or contact a Poison Control Center right away.

Do not use if tamper evident seal is broken or missing. Store in a cool, dry place.

DOSAGE AND ADMINISTRATION

DIRECTIONS: Feel the emotion fully, breathe deeply-connecting breaths. Put 5 drops under tongue to release emotion. Continue 5 drops 2x daily as needed. Consult a physician for use in children under 12 years of age.

INACTIVE INGREDIENTS: Demineralized water, 25% Alcohol.

QUESTIONS

MFG FOR:

Theresa Dale, N.D.

1237 S Victoria Ave.

Oxnard, CA 93035

1-866-962-6484

PACKAGE LABEL

Dr. Theresa Dale's

HOMEOPATHIC

Neuro-Emotional Remedies

#9 SPLEEN/PANCREAS

Low Self-Esteem

1 fl oz (30 ml)